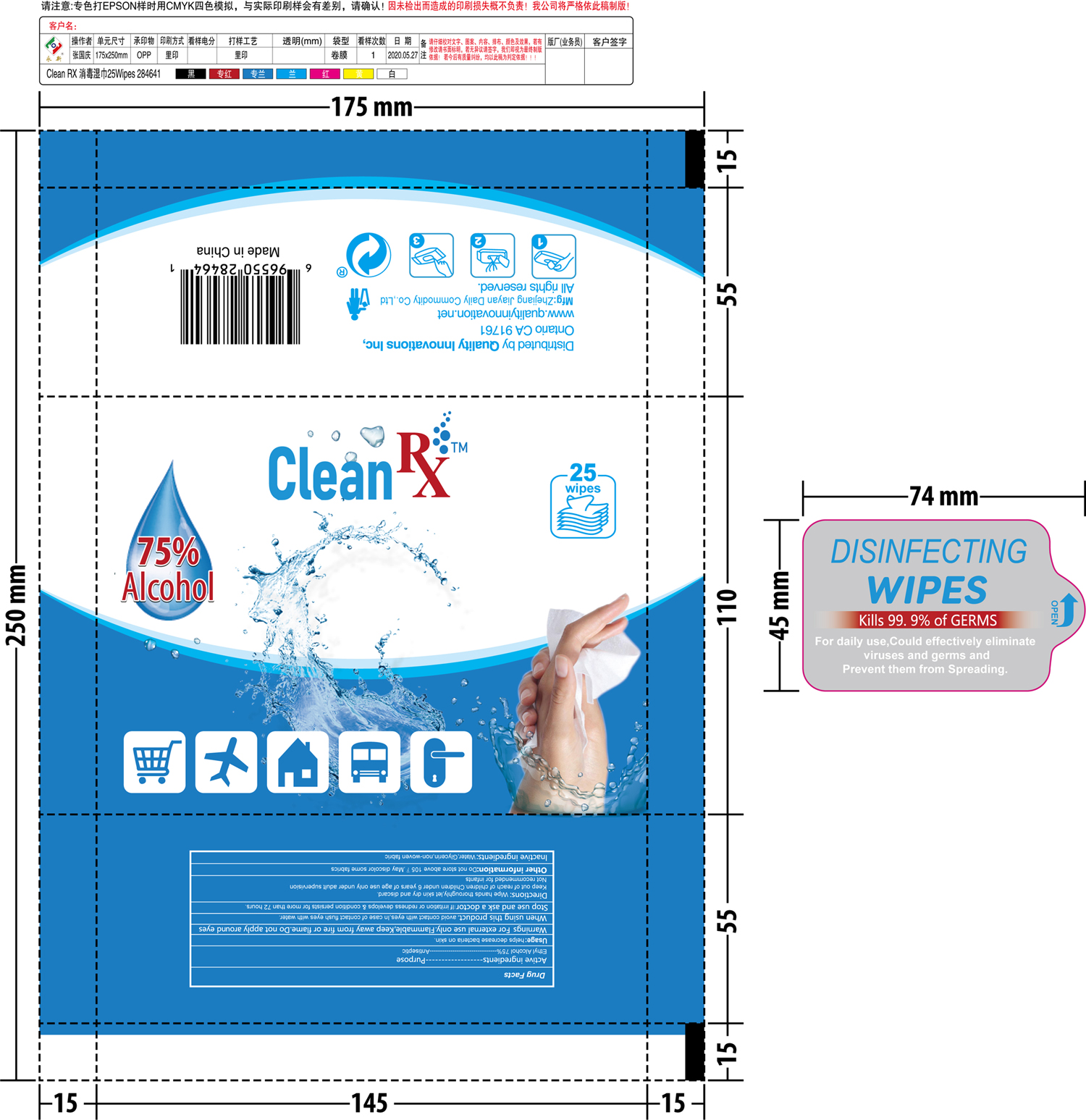 DRUG LABEL: sanitizing wipes
NDC: 74235-002 | Form: CLOTH
Manufacturer: Quality Innovations Inc.
Category: otc | Type: HUMAN OTC DRUG LABEL
Date: 20200625

ACTIVE INGREDIENTS: ALCOHOL 0.75 mL/1 1
INACTIVE INGREDIENTS: GLYCERIN; WATER

sanitizing wipes

Active Ingredient(s)

Alcohol 75% . Purpose: Antiseptic

Purpose

Antiseptic

Use

helps decrease bacteria on skin.

Warnings

For external use only. Flammable. Keep away from heat or flame. Do not apply around eyes.

When using this product

avoid contact with eyes. In case of contact flush eyes with water.

Stop use and ask a doctor

if irritation and redness develops & condition persists for more than 72 hours.

Keep out of reach of children. Children under 6 years of age use only under adult supervision.

Not recommended for infants

Directions

Wipe thoroughly, let skin dry and discard.

Other information

Do not store above 105F. May discolor some fabrics.

Inactive ingredients

water, glycerin

Package Label - Principal Display Panel

25 PCS NDC: 74235-002-01